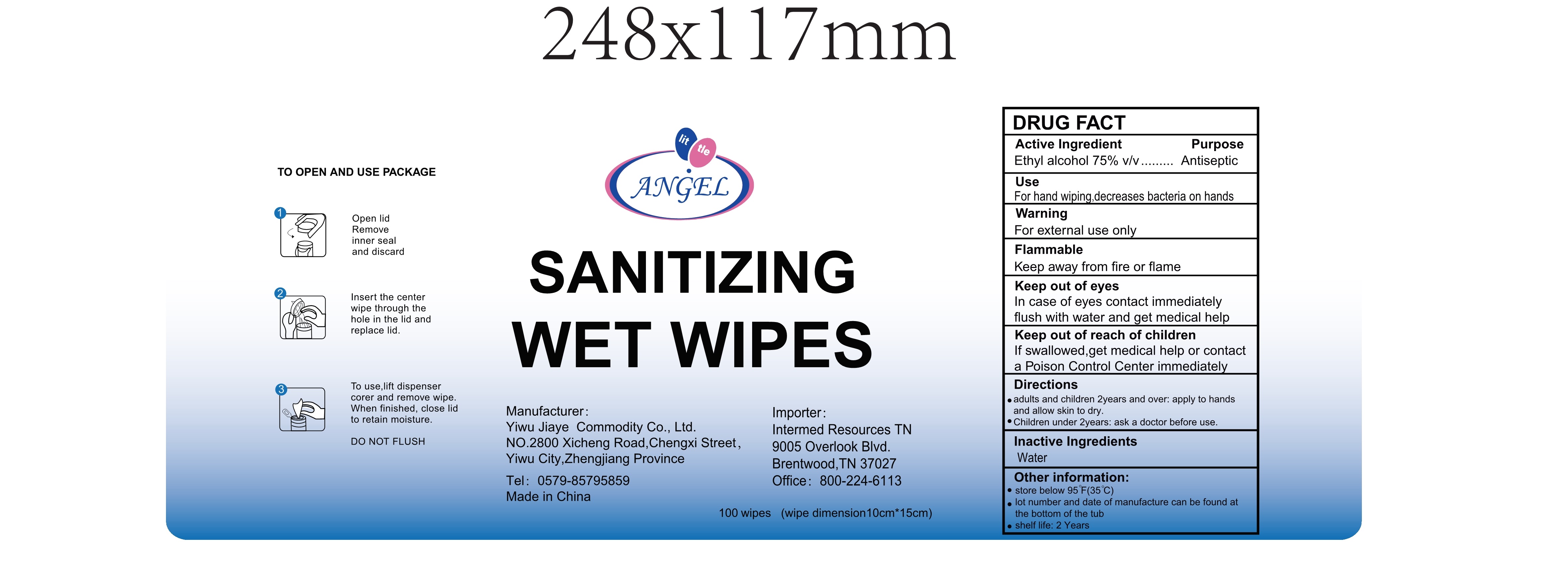 DRUG LABEL: SANITIZING WET WIPES
NDC: 55473-100 | Form: CLOTH
Manufacturer: Yiwu Jiaye Commodity Co., Ltd.
Category: otc | Type: HUMAN OTC DRUG LABEL
Date: 20201015

ACTIVE INGREDIENTS: ALCOHOL 2.35 mL/1 1
INACTIVE INGREDIENTS: WATER

55473-100 SANITIZING WET WIPES

Active Ingredient(s)

Alcohol 75% v/v. Purpose: Antiseptic

Purpose

Antiseptic, SANITIZING WET WIPES

Use

For hand wiping, decreases bacteria on hands.

Warnings

For external use only. Keep away from fire or flame. In case of eyes contact immediately flush with water and get medical help.

Do not use

- audults and children 2 years and over, apply to hands and allow skin to dry.
- Children under 2 years , ask a doctor before use.

When using this product keep out of eyes, ears, and mouth. In case of contact with eyes, rinse eyes thoroughly with water.
Stop use and ask a doctor if irritation or rash occurs. These may be signs of a serious condition.
Keep out of reach of children. If swallowed, get medical help or contact a Poison Control Center right away.

Stop use and ask a doctor if irritation or rash occurs. These may be signs of a serious condition.

Keep out of reach of children. If swallowed, get medical help or contact a Poison Control Center right away.

Directions

- 1. Open lid remove inner seal and discard.
- 2. Insert the center wipe through the hole in the lid and replace lid.
- 3. To use lift dispenser corer and remove wipe. When finished, colse lid to retain moisture.
- DO NOT FLUSH.

Other information

- Store between 95℉ (35℃).
- lot number and date of manufacture can be found at the bottom of the tub.
- shelf life: 2 Years.

Inactive ingredients

purified water USP

Package Label - Principal Display Panel

100 cloth in 1 pail NDC: 55473-100-01